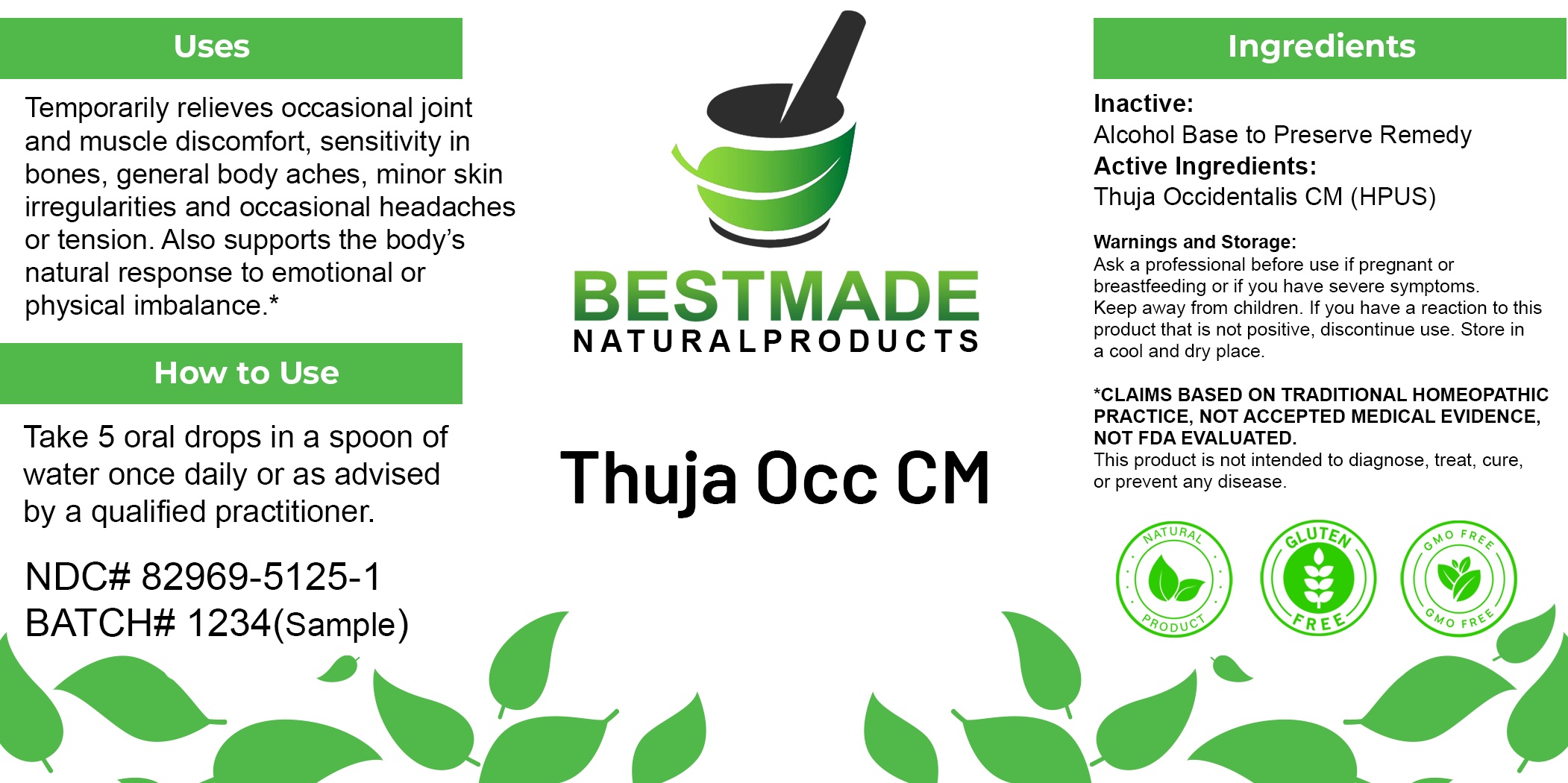 DRUG LABEL: Thuja Occ CM
NDC: 82969-5125 | Form: LIQUID
Manufacturer: Bestmade Natural Products
Category: homeopathic | Type: HUMAN OTC DRUG LABEL
Date: 20250605

ACTIVE INGREDIENTS: THUJA OCCIDENTALIS LEAFY TWIG 100000 [hp_C]/1 mL
INACTIVE INGREDIENTS: ALCOHOL 0.9 mL/1 mL

Thuja Occ CM

INACTIVE INGREDIENT

Alcohol base to preserved product.

Warnings and Storage:

This product is classified as a high-potency homeopathic remedy and is to be used as advised by health care professional. Ask a professional before use if pregnant or breastfeeding or if you have severe symptoms. Keep away from children. If you have a reaction to this product that is not positive, discontinue use. Store in a cool and dry place.

*CLAIMS BASED ON TRADITIONAL HOMEOPATHIC PRACTICE, NOT ACCEPTED MEDICAL EVIDENCE, NOT FDA EVALUATED. This product is not intended to diagnose, treat, cure, or prevent any disease.

KEEP OUT OF REACH OF CHILDREN

Warnings and Storage:

This product is classified as a high-potency homeopathic remedy and is to be used as advised by health care professional. Ask a professional before use if pregnant or breastfeeding or if you have severe symptoms. Keep away from children. If you have a reaction to this product that is not positive, discontinue use. Store in a cool and dry place.

*CLAIMS BASED ON TRADITIONAL HOMEOPATHIC PRACTICE, NOT ACCEPTED MEDICAL EVIDENCE, NOT FDA EVALUATED. This product is not intended to diagnose, treat, cure, or prevent any disease.

DOSAGE AND ADMINISTRATION

Dosage Instructions: Take 5 oral drops in a spoon of water once daily or as advised by a qualified practitioner.

INDICATIONS AND USAGE

Use: Temporarily relieves occasional joint and muscle discomfort, sensitivity in bones, general body aches, minor skin irregularities and occasional headaches or tension. Also supports the body’s natural response to emotional or physical imbalance.*

PURPOSE

Use: Temporarily relieves occasional joint and muscle discomfort, sensitivity in bones, general body aches, minor skin irregularities and occasional headaches or tension. Also supports the body’s natural response to emotional or physical imbalance.*

Active Ingredient: Thuja Occidentalis CM (HPUS)

Entire package label.